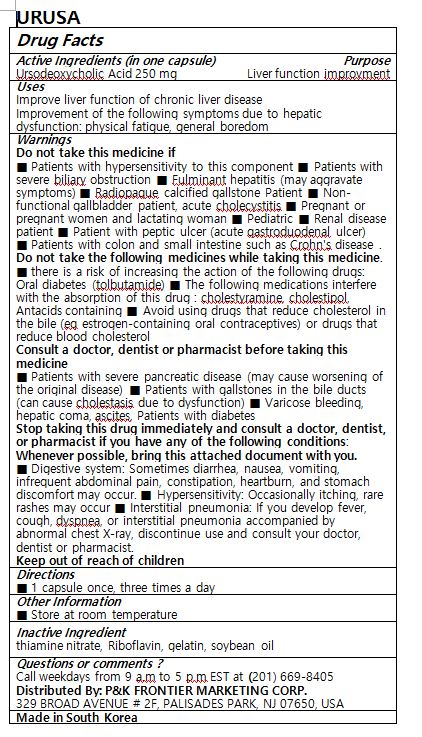 DRUG LABEL: URUSA
NDC: 72689-0001 | Form: CAPSULE
Manufacturer: OASIS TRADING
Category: otc | Type: HUMAN OTC DRUG LABEL
Date: 20181119

ACTIVE INGREDIENTS: URSODIOL 250 mg/1 1
INACTIVE INGREDIENTS: RIBOFLAVIN; GELATIN; SOYBEAN OIL; THIAMINE MONONITRATE

ACTIVE INGREDIENT

Ursodeoxycholic Acid

PURPOSE

Improve liver function of chronic liver disease

Improvement of the following symptoms due to hepatic dysfunction: physical fatigue, general boredom

Keep out of reach of children

INDICATIONS AND USAGE

1 capsule once, three times a day

WARNINGS

Do not take this medicine if

■ Patients with hypersensitivity to this component ■ Patients with severe biliary obstruction ■ Fulminant hepatitis (may aggravate symptoms) ■ Radiopaque calcified gallstone Patient ■ Non-functional gallbladder patient, acute cholecystitis ■ Pregnant or pregnant women and lactating woman ■ Pediatric ■ Renal disease patient ■ Patient with peptic ulcer (acute gastroduodenal ulcer)

■ Patients with colon and small intestine such as Crohn's disease .

Do not take the following medicines while taking this medicine.

■ there is a risk of increasing the action of the following drugs: Oral diabetes (tolbutamide) ■ The following medications interfere with the absorption of this drug : cholestyramine, cholestipol, Antacids containing ■ Avoid using drugs that reduce cholesterol in the bile (eg estrogen-containing oral contraceptives) or drugs that reduce blood cholesterol

Consult a doctor, dentist or pharmacist before taking this medicine

■ Patients with severe pancreatic disease (may cause worsening of the original disease) ■ Patients with gallstones in the bile ducts (can cause cholestasis due to dysfunction) ■ Varicose bleeding, hepatic coma, ascites, Patients with diabetes

Stop taking this drug immediately and consult a doctor, dentist, or pharmacist if you have any of the following conditions: Whenever possible, bring this attached document with you.

■ Digestive system: Sometimes diarrhea, nausea, vomiting, infrequent abdominal pain, constipation, heartburn, and stomach discomfort may occur. ■ Hypersensitivity: Occasionally itching, rare rashes may occur ■ Interstitial pneumonia: If you develop fever, cough, dyspnea, or interstitial pneumonia accompanied by abnormal chest X-ray, discontinue use and consult your doctor, dentist or pharmacist.

INACTIVE INGREDIENT

thiamine nitrate, Riboflavin, gelatin, soybean oil

DOSAGE AND ADMINISTRATION

For oral use only